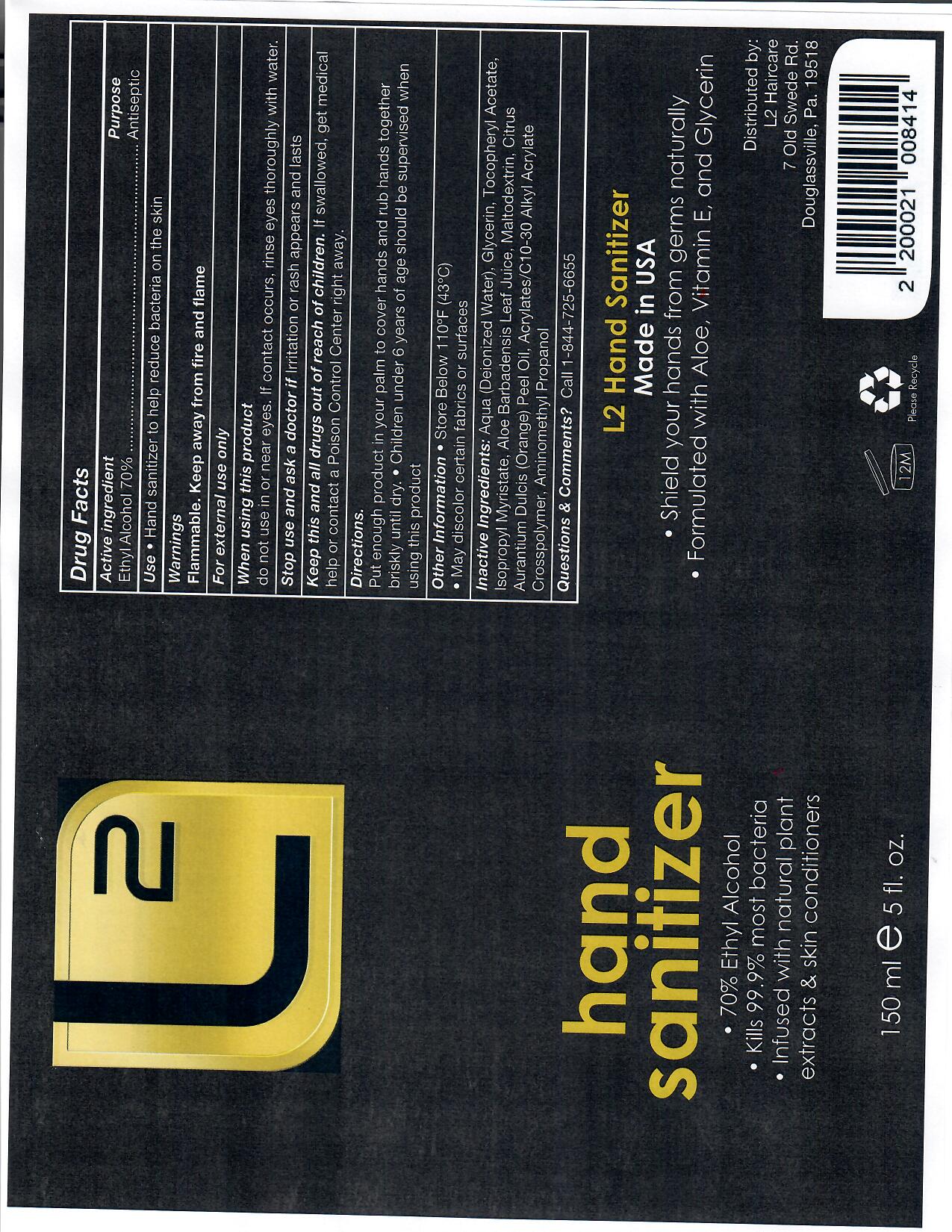 DRUG LABEL: HandSanitizer
NDC: 77826-112 | Form: SOLUTION
Manufacturer: Lords & Ladies Hair Nail & Skin Care
Category: otc | Type: HUMAN OTC DRUG LABEL
Date: 20200726

ACTIVE INGREDIENTS: ALCOHOL 70 mL/100 mL
INACTIVE INGREDIENTS: ISOPROPYL MYRISTATE; GLYCERIN; ALOE; WATER; MALTODEXTRIN; ORANGE PEEL

This is a hand sanitizer manufactured according to the Temporary Policy for Preparation of Certain Alcohol-Based Hand Sanitizer Products During the Public Health Emergency (CoViD-19); Guidance for Industry.

The hand sanitizer is manufactured using only the following United States Pharmacopoeia (USP) grade ingredients in the preparation of the product (percentage in final product formulation) consistent with World Health Organization (WHO) recommendations:

1. Alcohol (ethanol)
2. Sterile distilled water.

Active Ingredient(s)

Alcohol 70%. Purpose: Antiseptic

Purpose

Antiseptic, Hand Sanitizer

Use

Hand Sanitizer to help reduce bacteria on the skin.

Warnings

For external use only. Flammable. Keep away from fire and flame

Do not use in or near eyes

When using this product do not use in or near eyes. In case of contact with eyes, rinse eyes thoroughly with water.
Stop use and ask a doctor if irritation or rash occurs. These may be signs of a serious condition.
Keep out of reach of children. If swallowed, get medical help or contact a Poison Control Center right away.

Stop use and ask a doctor if irritation or rash occurs. These may be signs of a serious condition.

Keep out of reach of children. If swallowed, get medical help or contact a Poison Control Center right away.

Directions

- Put enough product in your palm to cover hands and rub hands together briskly until dry.
- Children under 6 years of age should be supervised when using this product.

Other information

- Store below 110F (43C)

Inactive ingredients

Deionized water, glycerin, tocopheryl acetate, isopropyl myristate, aloe barbadensis leaf juice, maltodextrin, citrus aurantium dulcis peel oil, acrylates/C10-30 Alkyl Acrylate Crosspolymer, Amminomethyl Propanol